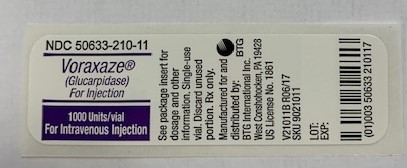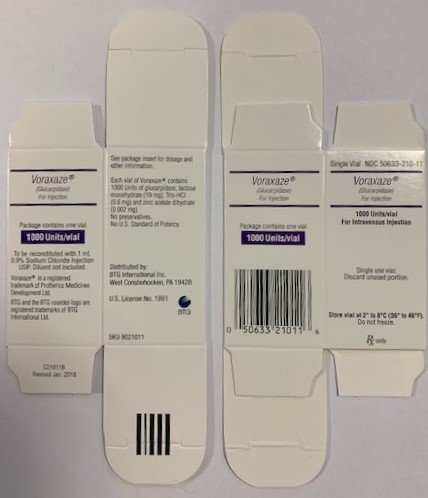 DRUG LABEL: Voraxaze
NDC: 50633-210 | Form: INJECTION, POWDER, FOR SOLUTION
Manufacturer: BTG International Inc.
Category: prescription | Type: HUMAN PRESCRIPTION DRUG LABEL
Date: 20241127

ACTIVE INGREDIENTS: GLUCARPIDASE 1000 [USP'U]/1 1
INACTIVE INGREDIENTS: LACTOSE MONOHYDRATE 10 mg/1 1; ZINC ACETATE 0.002 mg/1 1; TROMETHAMINE HYDROCHLORIDE 0.6 mg/1 1

HIGHLIGHTS OF PRESCRIBING INFORMATION

These highlights do not include all the information needed to use VORAXAZE®safely and effectively. See full prescribing information for VORAXAZE®.
VORAXAZE (glucarpidase) for injection, for intravenous use
Initial U.S. Approval: 2012

1 INDICATIONS AND USAGE

VORAXAZE is a carboxypeptidase indicated to reduce toxic plasma methotrexate concentration (greater than 1 micromole per liter) in adult and pediatric patients with delayed methotrexate clearance (plasma methotrexate concentrations greater than 2 standard deviations of the mean methotrexate excretion curve specific for the dose of methotrexate administered) due to impaired renal function. (1)

Limitations of Use:VORAXAZE is not recommended for use in patients who exhibit the expected clearance and expected plasma methotrexate concentration. Reducing plasma methotrexate concentration in these patients may result in subtherapeutic exposure to methotrexate. (1)

2 DOSAGE AND ADMINISTRATION

- The recommended dosage of VORAXAZE is 50 Units per kilogram as a single intravenous injection over 5 minutes. (2.1).
- For the first 48 hours after the dose of VORAXAZE, administer the same leucovorin dose given prior to VORAXAZE. Administer leucovorin at least 2 hours before or 2 hours after the dose of VORAXAZE. (2.2)
- Beyond 48 hours after the dose of VORAXAZE, administer leucovorin based on the measured methotrexate concentration. Continue leucovorin until the methotrexate concentration has been maintained below the leucovorin treatment threshold for a minimum of 3 days. (2.2)

3 DOSAGE FORMS AND STRENGTHS

For Injection: 1,000 Units as a lyophilized powder in a single-dose vial for reconstitution (3)

4 CONTRAINDICATIONS

None.

5 WARNINGS AND PRECAUTIONS

- Serious Hypersensitivity Reactions:Serious hypersensitivity reactions occurred. (5.1)
- Monitoring Methotrexate Concentration:Measure methotrexate concentrations within 48 hours following VORAXAZE administration using a chromatographic method; immunoassays are unreliable for samples collected within 48 hours following VORAXAZE administration. (5.2)

6 ADVERSE REACTIONS

The most common related adverse events (>1%) were paresthesia, flushing, nausea and/or vomiting, hypotension and headache. (6)

To report SUSPECTED ADVERSE REACTIONS, contact BTG at 877-377-3784 or FDA at 1-800-FDA-1088 or www.fda.gov/medwatch.

FULL PRESCRIBING INFORMATION

1 INDICATIONS AND USAGE

VORAXAZE is indicated to reduce toxic plasma methotrexate concentration (greater than 1 micromole per liter) in adult and pediatric patients with delayed methotrexate clearance (plasma methotrexate concentrations greater than 2 standard deviations of the mean methotrexate excretion curve specific for the dose of methotrexate administered) due to impaired renal function.

Limitations of Use:VORAXAZE is not recommended for use in patients who exhibit the expected clearance and expected plasma methotrexate concentration. Reducing plasma methotrexate concentration in these patients may result in subtherapeutic exposure to methotrexate [see Clinical Studies (14)] .

2 DOSAGE AND ADMINISTRATION

2.1 Recommended Dosage

The recommended dosage of VORAXAZE is 50 Units per kilogram (kg) as a single intravenous injection administered over 5 minutes. Flush intravenous line before and after administration.

2.2 Concomitant Use with Leucovorin Rescue

When administering VORAXAZE concomitantly with leucovorin, administer leucovorin at least 2 hours before or 2 hours after the VORAXAZE dose [see Drug Interactions (7.1)] .

For the first 48 hours after a dose of VORAXAZE:

- Administer the same leucovorin dosage given prior to the VORAXAZE dose.

Beyond 48 hours after a dose of VORAXAZE:

- Determine the leucovorin dosage based on the measured methotrexate concentration. Do not discontinue leucovorin based on the determination of a single methotrexate concentration below the leucovorin rescue threshold.
- Continue leucovorin until the methotrexate concentration has been maintained below the leucovorin rescue threshold for a minimum of 3 days.

Continue intravenous hydration and urinary alkalinization as indicated.

When measuring methotrexate concentrations following a VORAXAZE dose, a chromatographic method is preferred over an immunoassay [see Warnings and Precautions (5.2)] .

2.3 Preparation

Reconstitute the contents of the vial with 1 mL of 0.9% Sodium Chloride Injection, USP.

Roll and tilt the vial gently to mix. Do not shake.

Inspect the vial and discard VORAXAZE if the solution is not clear, colorless, and free of particulate matter.

Use reconstituted VORAXAZE immediately or store under refrigeration at 36° to 46°F (2° to 8°C) for up to 4 hours if not used immediately. VORAXAZE contains no preservative and is supplied as a single-dose vial. Discard any unused product.

3 DOSAGE FORMS AND STRENGTHS

For Injection: 1,000 Units as a white lyophilized powder in a single-dose vial for reconstitution.

4 CONTRAINDICATIONS

None.

5 WARNINGS AND PRECAUTIONS

5.1 Serious Hypersensitivity Reactions

Serious hypersensitivity reactions occurred in less than 1% of patients [ see Adverse Reactions (6.1) ].

5.2 Interference with Immunoassay Measurements of Methotrexate

DAMPA (4-deoxy-4-amino-N^10- methylpteroic acid), an inactive metabolite of methotrexate formed following VORAXAZE administration, interferes with the measurement of methotrexate concentration using immunoassays. This interference results in an overestimation of the methotrexate concentration. Based on the half-life of DAMPA (about 9 hours), VORAXAZE may interfere with the measurement of methotrexate concentration for up to 48 hours following a VORAXAZE dose [see Clinical Pharmacology (12.1) ].

When measuring methotrexate concentration following a VORAXAZE dose, a chromatographic method is preferred over an immunoassay.

6 ADVERSE REACTIONS

The following clinically significant adverse reactions are described elsewhere in the labeling:

- Serious Hypersensitivity Reactions [Warnings and Precautions (5.1)].

6.1 Clinical Trials Experience

Because clinical trials are conducted under controlled but widely varying conditions, adverse reaction rates observed in clinical trials of VORAXAZE cannot be directly compared to rates in the clinical trials of other drugs and may not reflect the rates observed in practice.

The evaluation of adverse reactions in patients who received VORAXAZE was confounded, because patients had toxic plasma methotrexate concentration due to prolonged methotrexate clearance, which is associated with myelosuppression, mucositis, acute hepatitis, and renal dysfunction and failure.

The safety of VORAXAZE is based on data from 290 patients who were enrolled in Study 1 or Study 2, two single-arm, open-label, multicenter studies conducted in patients who had markedly delayed methotrexate clearance due to impaired renal function. Patients with osteosarcoma were eligible for these studies if the plasma methotrexate concentration was >50 µmol/L at 24 hours, >5 µmol/L at 48 hours, or >2 standard deviations above the mean methotrexate elimination curve at least 12 hours after methotrexate administration; and there was a ≥2-fold increase in serum creatinine above baseline. All other patients were eligible for these studies if the plasma methotrexate concentration was >10 µmol/L more than 42 hours after the start of the methotrexate or the plasma methotrexate concentration was >2 standard deviations above the mean methotrexate excretion curve at least 12 hours following methotrexate; and the serum creatinine was >1.5 times the upper limit of normal (ULN) or the creatinine clearance (CLcr) was <60 mL/min at least 12 hours following methotrexate administration.

Safety data was available for 149 patients enrolled in Study 1. The protocol specified that patients with pre-VORAXAZE methotrexate concentration >100 μmol/L were to receive a second VORAXAZE dose 48 hours after the first dose; that patients continue receiving intravenous hydration, urinary alkalinization and leucovorin; and that leucovorin administration be adjusted to ensure that it was not administered within 2 hours before or after a VORAXAZE dose. VORAXAZE-related adverse reactions were collected on a flow sheet with a daily log of adverse reactions characterized as “glucarpidase toxicity”. Additional safety information was collected from clinical records submitted by treating physicians. This safety information was abstracted and categorized using the National Cancer Institute (NCI) Common Terminology Criteria for Adverse Events (CTCAE) version 3. One (n=106) or 2 (n= 30) doses of VORAXAZE were administered; the number of doses was not specified for 13 patients. Doses ranged from 18 Units/kg to 98 Units/kg, with a median dose of 49 Units/kg. The median age was 18 years (1 month to 85 years); 63% were male; and the underlying malignancies were osteosarcoma/sarcomas in 32% and leukemia or lymphoma in 63% of patients.

Safety data was available for 141 patients enrolled in Study 2. The protocol did not specify the criterion for allowing patients to receive a second VORAXAZE dose. The protocol specified that patients continue receiving intravenous hydration, urinary alkalinization and leucovorin and that leucovorin administration be adjusted to ensure that it was not administered within 2 hours before or after VORAXAZE. VORAXAZE-related adverse reactions were collected and severity was graded according to NCI CTCAE version 3. One (n=122) or 2 (n= 18) doses of VORAXAZE were administered; the number of doses was not specified for 1 patient. Doses ranged from 6 Units/kg to 189 Units/kg, with a median dose of 50 Units/kg. The median age was 17 years (6 months to 85 years); 64% were male; and the underlying malignancies were osteogenic sarcoma in 32% and leukemia or lymphoma in 62% of patients.

Among the 290 patients, 8 deaths occurred within 30 days of VORAXAZE exposure that were not related to progressive disease.

The most common adverse reactions (reported in >1%) were paresthesia, flushing, and nausea and/or vomiting. Table 1summarizes select adverse reactions; adverse reactions likely associated with toxic methotrexate plasma concentrations, such as hematological, renal and hepatic adverse reactions, were not included in this table.

Table 1: Select Adverse Reactions Occurring in Patients Receiving VORAXAZE in Study 1 and Study 2
Adverse Reaction | VORAXAZE N= 290
Adverse Reaction | Grades 1 and 2^2(%)
Paresthesia | 2
Flushing^1,2 | 2
Nausea/Vomiting | 2
Headache | 1
Hypotension | 1
Blurred Vision | <1
Diarrhea | <1
Hypersensitivity | <1
Hypertension | <1
Rash | <1
Throat irritation/Throat tightness | <1
Tremor | <1
^1This incidence includes the following terms: flushing, feeling hot, burning sensation.
^2One of these reactions was classified as Grade 3.

6.2 Immunogenicity

As with all therapeutic proteins, there is potential for immunogenicity. The detection of antibody formation is highly dependent on the sensitivity and specificity of the assay. Additionally, the observed incidence of antibody (including neutralizing antibody) positivity in an assay may be influenced by several factors, including assay methodology, sample handling, timing of sample collection, concomitant medications, and underlying disease. For these reasons, comparison of incidence of antibodies in the studies described below with the incidence of antibodies in other studies or to other glucarpidase products may be misleading.

In clinical trials, 121 patients who received one (n=99), 2 (n=21), or 3 (n=1) doses of VORAXAZE were evaluated for anti-glucarpidase antibodies. Twenty-five of these 121 patients (21%) had detectable anti-glucarpidase antibodies following VORAXAZE administration, of which 19 received 1 dose of VORAXAZE and 6 received 2 doses of VORAXAZE. Antibody titers were determined using a bridging enzyme-linked immunosorbent assay (ELISA) for anti- glucarpidase antibodies.

Neutralizing antibodies were detected in 11 of the 25 patients who tested positive for anti- glucarpidase binding antibodies. Eight of these 11 patients had received a single dose of VORAXAZE; however, the development of neutralizing antibodies may be underreported due to lack of assay sensitivity.

7 DRUG INTERACTIONS

7.1 Effects of VORAXAZE on Leucovorin

VORAXAZE can decrease leucovorin concentration, which may decrease the effect of leucovorin rescue unless leucovorin is dosed as recommended [see Dosage and Administration (2.2), Clinical Pharmacology (12.3)] .

VORAXAZE may also reduce the concentrations other folate analogs or folate analog metabolic inhibitors.

7.2 Effect of VORAXAZE on Measurement of Methotrexate Concentration

DAMPA (4-deoxy-4-amino-N10- methylpteroic acid), an inactive metabolite of methotrexate formed following VORAXAZE administration, interferes with the measurement of methotrexate concentration using immunoassays. This interference results in an overestimation of the methotrexate concentration. Based on the half-life of DAMPA, VORAXAZE may interfere with the measurement of methotrexate concentrations for approximately 48 hours following a VORAXAZE dose [see Warnings and Precautions (5.2)] .

When measuring methotrexate concentration following a VORAXAZE dose, a chromatographic method is preferred over an immunoassay.

8 USE IN SPECIFIC POPULATIONS

8.1 Pregnancy

Risk Summary

There are no available data on VORAXAZE use in pregnant women or animal reproduction studies to evaluate for a drug-associated risk of major birth defects, miscarriage or adverse maternal or fetal outcomes.

VORAXAZE is administered in combination with methotrexate, which can cause embryo-fetal harm. Refer to methotrexate prescribing information for additional information.

In the U.S. general population, the estimated background risk of major birth defects and miscarriage in clinically recognized pregnancies is 2% to 4% and 15% to 20%, respectively.

8.2 Lactation

Risk Summary

There are no data on the presence of glucarpidase in human milk or its effects on the breastfed infant or on milk production.

VORAXAZE is administered in combination with methotrexate. Refer to methotrexate prescribing information for additional information.

8.4 Pediatric Use

The safety and effectiveness of VORAXAZE have been established in pediatric patients. Use of VORAXAZE for this indication is supported by evidence from a single-arm, open-label study in adult and pediatric patients 5 years of age and older with additional safety data in pediatric patients 1 to 17 years of age as described below.

Of the 22 patients in the efficacy dataset in Study 1, 12 were pediatric patients with ages ranging from 5 years to 16 years. Three of the 6 pediatric patients with a pre-VORAXAZE methotrexate concentration of 1 μmol/L to 50 μmol/L achieved a rapid and sustained clinically important reduction (RSCIR) in plasma methotrexate concentration, while none of the 6 pediatric patients with a pre-VORAXAZE methotrexate concentration >50 μmol/L achieved a RSCIR [see Clinical Studies (14)] .

One-hundred forty-seven pediatric patients from 1 month to 17 years received VORAXAZE in Study 1 and Study 2 [see Adverse Reactions (6.1)] . No overall differences in safety were observed between these patients and adult patients.

8.5 Geriatric Use

Of the total number of 290 patients in clinical studies of VORAXAZE, 15% were 65 and over, while 4% were 75 and over. No overall differences in safety or effectiveness were observed between these patients and younger adult patients.

8.6 Renal Impairment

A study of the pharmacokinetics of glucarpidase in the absence of methotrexate in 4 subjects with severe renal impairment (CLcr <30 mL/min) showed that the mean pharmacokinetic parameters were similar to those observed in healthy subjects.

On this basis, no dose adjustment of VORAXAZE is recommended for patients with renal impairment [see Clinical Pharmacology (12.3)].

11 DESCRIPTION

Glucarpidase is a carboxypeptidase produced by recombinant DNA technology in genetically modified Escherichia coli.Glucarpidase is a 390-amino acid homodimer protein with a molecular weight of 83 kDa. Each potency Unit corresponds to the enzymatic cleavage of 1 µmol/L of methotrexate per minute at 37°C.

VORAXAZE (glucarpidase) for injection, for intravenous use is supplied as a sterile, preservative-free, white lyophilized powder in single-dose vials. Each vial contains 1,000 Units of glucarpidase, lactose monohydrate (10 mg), Tris-HCl (0.6 mg) and zinc acetate dihydrate (0.002 mg).

12 CLINICAL PHARMACOLOGY

12.1 Mechanism of Action

Glucarpidase is a recombinant bacterial enzyme that hydrolyzes the carboxyl- terminal glutamate residue from folic acid and classical antifolates such as methotrexate.

Glucarpidase converts methotrexate to its inactive metabolites 4-deoxy-4-amino-N^10- methylpteroic acid (DAMPA) and glutamate. VORAXAZE provides an alternate non-renal pathway for methotrexate elimination in patients with renal dysfunction during high-dose methotrexate treatment.

12.2 Pharmacodynamics

Following administration of VORAXAZE 50 Units/kg to patients in Study 1, methotrexate concentration measured by a chromatographic method was reduced by ≥ 97% within 15 minutes in all 22 treatment-evaluable patients and was maintained at a > 95% reduction up to 8 days in 20 of the 22 patients [see Clinical Studies (14)] .

12.3 Pharmacokinetics

The pharmacokinetics of glucarpidase in the absence of methotrexate were studied in 8 healthy subjects following VORAXAZE 50 Units/kg administered as an intravenous injection over 5 minutes. Serum glucarpidase activity levels were measured by an enzymatic assay and serum total glucarpidase concentrations were measured by ELISA. The mean Cmaxwas 3.3 μg/mL and the mean area under the curve (AUC0-INF) was 23.3 μg·h/mL. The pharmacokinetic parameters derived from the serum total glucarpidase concentrations were similar to those generated by serum glucarpidase activity levels except for elimination half-life as described below.

Distribution

The mean volume of distribution (Vd) was 3.6 L.

Elimination

Serum glucarpidase activity levels declined with a mean elimination half-life (t1/2) of 5.6 hours and serum total glucarpidase concentration declined with a mean elimination half-life of 9 hours. The mean systemic clearance (CL) was 7.5 mL/min.

Specific Populations

Patients with Renal Impairment

The pharmacokinetics of glucarpidase in the absence of methotrexate were studied in 4 subjects with severe renal impairment (CLcr <30 mL/min). Following a dose of VORAXAZE of 50 Units/kg, the mean pharmacokinetic parameters were similar to those observed in healthy subjects except for a longer half-life of 8.2 hours in subjects with severe renal impairment as compared to 5.6 hours in healthy subjects using an enzymatic assay to measure serum glucarpidase activity levels.

Drug Interaction Studies

In patients with cancer receiving high-dose methotrexate (≥1 g/m^2) and leucovorin rescue, a VORAXAZE dose of 50 Units/kg administered intravenously 2 hours before leucovorin, reduced (6S)-leucovorin AUC0-3hby 33% and Cmaxby 52% and reduced its active metabolite (6S)-5-methyltetrahydrofolate AUC0-3hby 92% and Cmaxby 93% [see Drug Interactions (7.1)] .

13 NONCLINICAL TOXICOLOGY

13.1 Carcinogenesis, Mutagenesis, Impairment of Fertility

Glucarpidase has not been evaluated in animals for carcinogenic or mutagenic potential or for impairment of fertility.

14 CLINICAL STUDIES

The efficacy of VORAXAZE was evaluated in a subset of 22 patients enrolled in Study 1 (NCT00001298), a single-arm, open-label study in patients who had markedly delayed methotrexate clearance (defined as more than 2 standard deviations greater than the mean excretion curve for methotrexate) due to impaired renal function. All patients received VORAXAZE 50 Units/kg as an intravenous injection over 5 minutes; those patients with pre-VORAXAZE methotrexate concentration >100 μmol/L were to receive a second dose of VORAXAZE 48 hours after the first dose. The protocol specified that patients continue receiving intravenous hydration, urinary alkalinization and leucovorin and that leucovorin administration be adjusted to ensure that it was not administered within 2 hours before or after VORAXAZE. These 22 patients had a pre-VORAXAZE methotrexate concentration >1 μmol/L and both pre- and post-treatment plasma samples available for determination of methotrexate concentration by a chromatographic method. The main outcome measure was the proportion of patients who achieved a rapid and sustained clinically important reduction (RSCIR) in plasma methotrexate concentration, defined as an attainment of plasma methotrexate concentration ≤1 μmol/L at 15 minutes that was sustained for up to 8 days following the initial injection.

The median age was 15.5 years (5 to 84 years); 59% were male; and the most common underlying cancers were osteogenic sarcoma (50%) and leukemia or lymphoma (45%).

Ten of the 22 patients achieved a RSCIR [45% (95% CI: 27%, 65%)]. Of the 12 patients who failed to achieve RSCIR, 5 patients (23%) attained a transient plasma methotrexate concentration ≤1 μmol/L. In these 5 patients, the median increase of plasma methotrexate concentration from their nadir was 1.4 μmol/L (0.3 to 2.5 μmol/L).

Table 2 summarizes the results of RSCIR and exploratory analyses following the first dose of VORAXAZE. An exploratory analysis in subgroups determined by pre-VORAXAZE methotrexate concentration suggests that the likelihood of attaining a RSCIR following the first VORAXAZE dose correlates with the pre-VORAXAZE methotrexate concentration. An additional exploratory analysis showed that all 9 patients with pre-VORAXAZE methotrexate concentration >50 μmol/L achieved >95% reduction in methotrexate concentration for up to 8 days following the first VORAXAZE dose although none of them achieved a RSCIR.

Table 2: Efficacy Results Following the First VORAXAZE Dose in Study 1
Pre-VORAXAZE Methotrexate Concentration (μmol/L) | Patients n | Patients Achieving RSCIR n (%) | Patients with >95% Rapid Reduction in Methotrexate Concentration and Maintained up to 8 Days n (%)
>1 | 22 | 10 (45%) | 20 (91%)
>1 to ≤50 | 13 | 10 (77%) | 11 (85%)
>50 to ≤100 | 2 | 0 | 2 (100%)
>100 | 7 | 0 | 7 (100%)
RSCIR: rapid and sustained clinically important reduction in methotrexate concentration.

Lack of Efficacy with a Second Dose of VORAXAZE

Six of the 7 patients with pre-first dose VORAXAZE methotrexate concentration >100 μmol/L received a second VORAXAZE dose of 50 Units/kg administered 48 hours after the first dose. Among them, none of the 4 patients with pre-second dose VORAXAZE methotrexate concentration >1 μmol/L achieved a RSCIR. The remaining 2 patients achieved a RSCIR, but their pre-second dose VORAXAZE methotrexate concentration were already ≤1 μmol/L.

Deaths Attributable to Methotrexate Toxicity

There are no controlled trials comparing VORAXAZE and supportive care to supportive care alone in patients with toxic plasma methotrexate concentration due to impaired renal function; therefore, there are no data regarding the effect of VORAXAZE on survival or toxic deaths due to methotrexate. VORAXAZE did not prevent fatal methotrexate toxicity in 3% of patients in the safety population.

16 HOW SUPPLIED/STORAGE AND HANDLING

VORAXAZE (glucarpidase) for injection is supplied as a sterile, preservative-free white lyophilized powder in an individually packaged glass single-dose vial closed with a bromo butyl elastomeric stopper and blue flip-off seal.

1,000 Units of glucarpidase per vial (1 vial per carton) NDC 50633-210-11

Store VORAXAZE refrigerated at 36°F to 46°F (2°C to 8°C). Do not freeze. Do not use VORAXAZE after the expiration date on the vial.

17 PATIENT COUNSELING INFORMATION

Serious Hypersensitivity Reactions

Inform patients that hypersensitivity reactions, including potentially serious reactions, may occur following a dose of VORAXAZE and to immediately report any signs and symptoms of infusion reactions [see Warnings and Precautions (5.1)] .

Administration

Inform patients of the importance of continued monitoring of plasma methotrexate concentration and renal function at the appropriate times after discharge from the hospital [see Warnings and Precautions (5.2)] .

Manufactured and distributed by:
BTG International Inc.
West Conshohocken, PA 19428

U.S. license 1861

VORAXAZE®is a registered trademark of Protherics Medicines Development

Ltd. BTG and the BTG roundel logo are registered trademarks of BTG

International Ltd.

P21011D

Package Label - Principal Display Panel - VORAXAZE Vial

Package Label - Principal Display Panel - VORAXAZE Carton